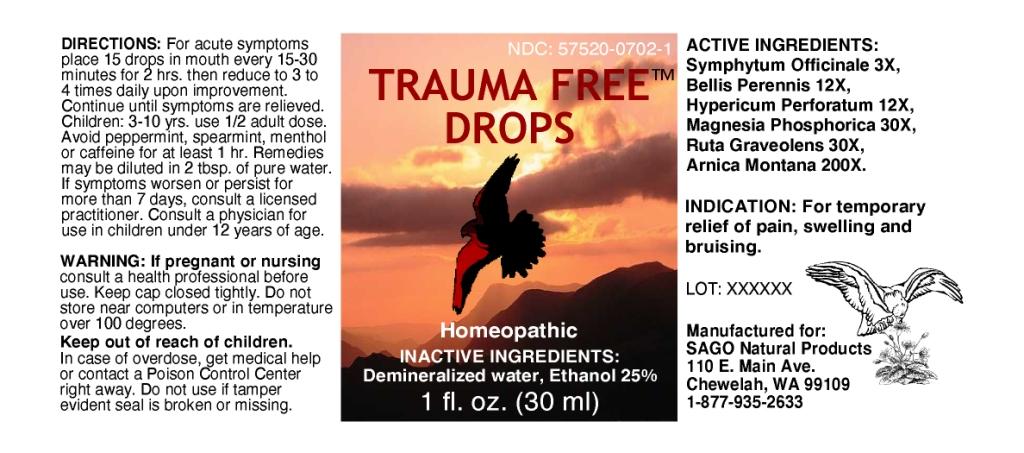 DRUG LABEL: Trauma Free
NDC: 57520-0702 | Form: LIQUID
Manufacturer: Apotheca Company
Category: homeopathic | Type: HUMAN OTC DRUG LABEL
Date: 20110601

ACTIVE INGREDIENTS: COMFREY ROOT 3 [hp_X]/1 mL; BELLIS PERENNIS 12 [hp_X]/1 mL; HYPERICUM PERFORATUM 12 [hp_X]/1 mL; MAGNESIUM PHOSPHATE, DIBASIC TRIHYDRATE 30 [hp_X]/1 mL; RUTA GRAVEOLENS FLOWERING TOP 30 [hp_X]/1 mL; ARNICA MONTANA 200 [hp_X]/1 mL
INACTIVE INGREDIENTS: WATER; ALCOHOL

Trauma Free Drops

ACTIVE INGREDIENT

ACTIVE INGREDIENTS: Symphytum officinale 3X, Bellis perennis 12X, Hypericum perforatum 12X, Magnesia phosphorica 30X, Ruta graveolens 30X, Arnica montana 200X.

PURPOSE

INDICATIONS: For temporary relief of pain, swelling and bruising.

WARNINGS

WARNINGS: If pregnant or nursing consult a health professional before use.

Keep cap closed tightly.

Do not store near computers or in temperature over 100 degrees.

Keep out of reach of children. In case of overdose, get medical help or contact a Poison Control Center right away.

Do not use if tamper evident seal is broken or missing.

DOSAGE AND ADMINISTRATION

DIRECTIONS: For acute symptoms place 15 drops in mouth every 15-30 minutes for 2 hrs. then reduce to 3 to 4 times daily upon improvement. Continue until symptoms aer relieved.

Children: 3-10 yrs. use 1/2 adult dose.

Avoid peppermint, spearmint, menthol or caffeine for at least 1 hr. Remedies may be diluted in 2 tbsp. of pure water. If symptoms worsen or persist for more than 7 days, consult a licensed practitioner. Consult a physician for use in children under 12 years of age.

INACTIVE INGREDIENTS: Demineralized water, Ethanol 25%.

KEEP OUT OF REACH OF CHILDREN. In case of overdose, get medical help or contact a Poison Control Center right away.

INDICATIONS AND USAGE

INDICATIONS: For temporary relief of pain, swelling and bruising.

QUESTIONS

Manufactured for:

SAGO Natural Products

110 E. Main Ave.

Chewelah, WA 99109

1-877-935-2633

PACKAGE LABEL

NDC: 57520-0702-1

TRAUMA FREE DROPS

Homeopathic

1 fl. oz. (30 ml)